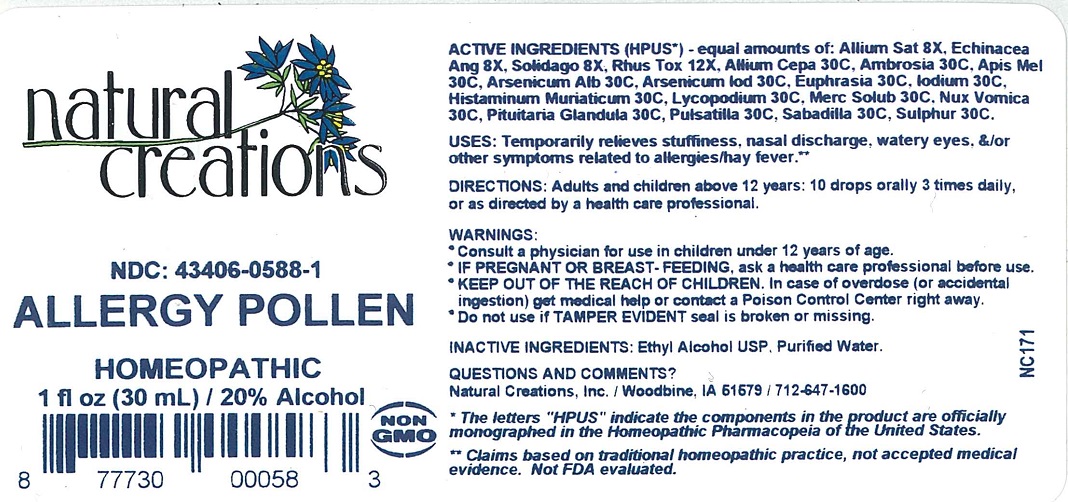 DRUG LABEL: ALLERGY POLLEN
NDC: 43406-0588 | Form: LIQUID
Manufacturer: Natural Creations, Inc.
Category: homeopathic | Type: HUMAN OTC DRUG LABEL
Date: 20220211

ACTIVE INGREDIENTS: GARLIC 8 [hp_X]/1 mL; ECHINACEA ANGUSTIFOLIA 8 [hp_X]/1 mL; SOLIDAGO VIRGAUREA FLOWERING TOP 8 [hp_X]/1 mL; TOXICODENDRON PUBESCENS LEAF 12 [hp_X]/1 mL; ONION 30 [hp_C]/1 mL; AMBROSIA ARTEMISIIFOLIA 30 [hp_C]/1 mL; APIS MELLIFERA 30 [hp_C]/1 mL; ARSENIC TRIOXIDE 30 [hp_C]/1 mL; ARSENIC TRIIODIDE 30 [hp_C]/1 mL; EUPHRASIA STRICTA 30 [hp_C]/1 mL; IODINE 30 [hp_C]/1 mL; HISTAMINE DIHYDROCHLORIDE 30 [hp_C]/1 mL; LYCOPODIUM CLAVATUM SPORE 30 [hp_C]/1 mL; MERCURIUS SOLUBILIS 30 [hp_C]/1 mL; STRYCHNOS NUX-VOMICA SEED 30 [hp_C]/1 mL; SUS SCROFA PITUITARY GLAND, POSTERIOR 30 [hp_C]/1 mL; ANEMONE PULSATILLA 30 [hp_C]/1 mL; SCHOENOCAULON OFFICINALE SEED 30 [hp_C]/1 mL; SULFUR 30 [hp_C]/1 mL
INACTIVE INGREDIENTS: ALCOHOL; WATER

ALLERGY POLLEN

ACTIVE INGREDIENT

Active Ingredients (HPUS*) - equal amounts of: Allium Sat 8X, Echinacea Ang 8X, Solidago 8X, Rhus Tox 12X, Allium Cepa 30C, Ambrosia 30C, Apis Mel 30C, Arsenicum Alb 30C, Euphrasia 30C, Iodium 30C, Histaminum Muriaticum 30C, Lycopodium 30C, Merc Solub 30C, Nux Vomica 30C, Pituitaria Glandula 30C, Pulsatilla 30C, Sabadilla 30C, Sulphur 30C.

PURPOSE

Uses: Temporarily relieves stuffiness, nasal discharge, watery eyes, &/or other symptoms related to allergies/hay fever.**

INDICATIONS AND USAGE

Uses: Temporarily relieves stuffiness, nasal discharge, watery eyes, &/or other symptoms related to allergies/hay fever.**

DOSAGE AND ADMINISTRATION

Directions: Adults & children above 12 years: 10 drops orally 3 times daily, or as directed by a health care professional.

KEEP OUT OF REACH OF CHILDREN

KEEP OUT OF THE REACH OF CHILDREN. In case of overdose (or accidental ingestion) get medical help or contact a Poison Control Center right away.

WARNINGS:

- Consult a physician for use in children under 12 years of age.
- IF PREGNANT OR BREAST-FEEDING, ask a health care professional before use.
- KEEP OUT OF THE REACH OF CHILDREN. In case of overdose (or accidental ingestion) get medical help or contact a Poison Control Center right away.
- Do not use if TAMPER EVIDENT seal is broken or missing.

Inactive Ingredients: Ethyl Alcohol USP, Purified Water.

Questions & Comments?

Natural Creations, Inc. / Woodbine, IA 51579 / 712-647-1600

REFERENCES

*The letters "HPUS" indicate the components in this product are officially monographed in the Homeopathic Pharmacopeia of the United States.

** Claims based on traditional homeopathic practice, not accepted medical evidence. Not FDA evaluated.

PACKAGE LABEL

NDC: 43406-0588-1

ALLERGY POLLEN

HOMEOPATHIC

1 fl oz (30 mL) / 20% Alcohol

UPC: 877730000583 NON GMO Logo